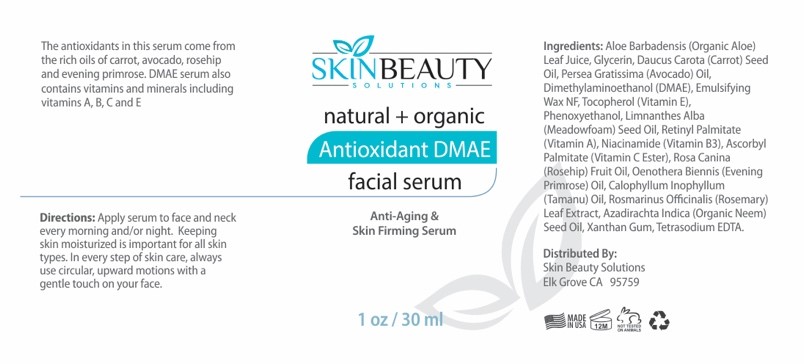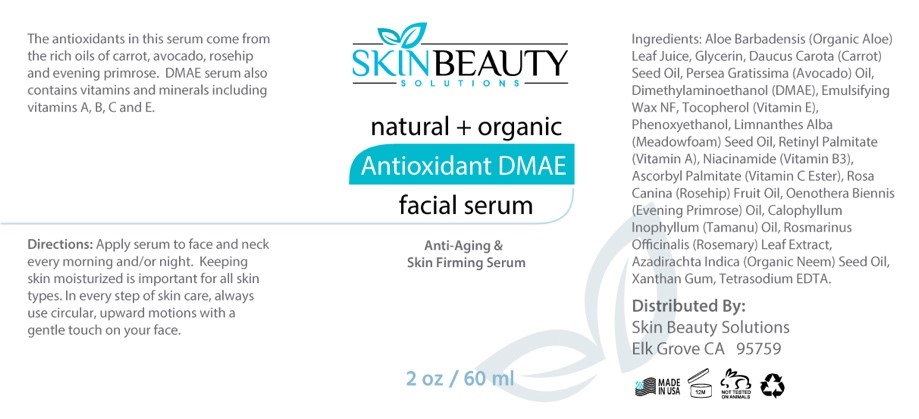 DRUG LABEL: Anti-Aging DMAE Face Serum
NDC: 84785-0055 | Form: SOLUTION
Manufacturer: Gazebo Wellness SKIN LLC
Category: otc | Type: HUMAN OTC DRUG LABEL
Date: 20241218

ACTIVE INGREDIENTS: EVENING PRIMROSE OIL 0.3 mg/30 mL; MEADOWFOAM SEED OIL 0.3 mg/30 mL; VITAMIN A 0.3 mg/30 mL; AVOCADO OIL 0.3 mg/30 mL; CARROT SEED OIL 0.3 mg/30 mL; TAMANU OIL 0.3 mg/30 mL; NIACINAMIDE 0.3 mg/30 mL; ASCORBYL PALMITATE 0.3 mg/30 mL; ALOE VERA LEAF 0.3 mg/30 mL; ROSEMARY 0.3 mg/30 mL
INACTIVE INGREDIENTS: XANTHAN GUM; TETRASODIUM EDETATE DIHYDRATE; GLYCERIN; PHENOXYETHANOL; VITAMIN E POLYETHYLENE GLYCOL SUCCINATE 0.3 mg/30 mL

DOSAGE AND ADMINISTRATION

The antioxidants in this serum come from the rich oils of carrot, avocado, rosehip and evening primrose. DMAE serum also contains vitamins and minerals including vitamins A, B, C and E

WARNINGS

Directions: Apply serum to face and neck every morning and/or night. Keeping skin moisturized is important for all skin types. In every step of skin care, always use circular, upward motions with a gentle touch on your face.

INACTIVE INGREDIENT

Inactive ingredients: Glycerin, Emulsifying Wax NF, Phenoxyethanol, Xanthan Gum, Tetrasodium EDTA, Organic Neem Seed Oil.

INDICATIONS AND USAGE

Apply serum to face and neck every morning and/or night. Keeping skin moisturized is important for all skin types. In every step of skin care, always use circular, upward motions with a gentle touch on your face.

keep out of reach of children

PURPOSE

SKINBEAUTY
SOLUTION
natural + organic Antioxidant DMAE facial serum
Anti-Aging &
Skin Firming Serum
1 oz/30 ml

ACTIVE INGREDIENT

Active ingredients: Aloe Vera Leaf Juice, Carrot Seed Oil, Avocado Oil, DMAE, Vitamin E, Meadowfoam Seed Oil, Vitamin A, Niacinamide, Vitamin C Ester, Rosehip Fruit Oil, Evening Primrose Oil, Tamanu Oil, Rosemary Leaf Extract.

PACKAGE LABEL

Content of labeling